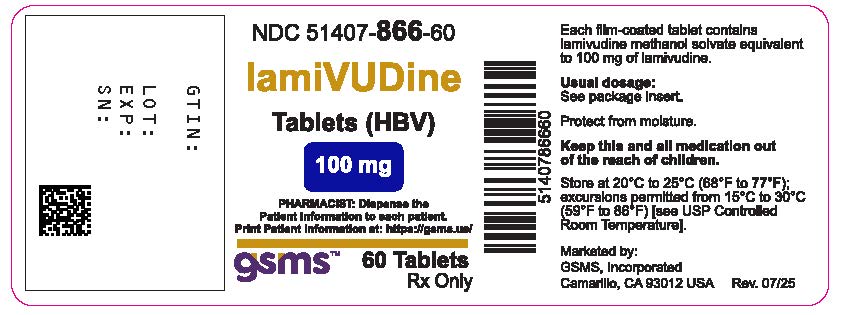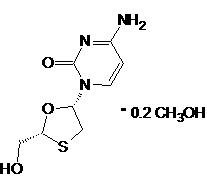 DRUG LABEL: Lamivudine
NDC: 51407-866 | Form: TABLET, FILM COATED
Manufacturer: Golden State Medical Supply, Inc.
Category: prescription | Type: HUMAN PRESCRIPTION DRUG LABEL
Date: 20250812

ACTIVE INGREDIENTS: LAMIVUDINE 100 mg/1 1
INACTIVE INGREDIENTS: ANHYDROUS LACTOSE; CROSPOVIDONE (120 .MU.M); SILICON DIOXIDE; MAGNESIUM STEARATE; HYPROMELLOSE 2910 (5 MPA.S); HYDROXYPROPYL CELLULOSE (1600000 WAMW); POLYETHYLENE GLYCOL 8000; TITANIUM DIOXIDE; FERRIC OXIDE RED; FERRIC OXIDE YELLOW

HIGHLIGHTS OF PRESCRIBING INFORMATION

LAMIVUDINE TABLETS (HBV). These highlights do not include all the information needed to use LAMIVUDINE TABLETS (HBV) safely and effectively. See full prescribing information for LAMIVUDINE TABLETS (HBV).
LAMIVUDINE tablets (HBV) for oral use
Initial U.S. Approval:1995

WARNING: EXACERBATIONS OF HEPATITIS B, AND RISK OF HIV-1 RESISTANCE IF LAMIVUDINE TABLETS (HBV) IS USED IN PATIENTS WITH UNRECOGNIZED OR UNTREATED HIV-1 INFECTION

See full prescribing information for complete boxed warning

- Severe acute exacerbations of hepatitis B have been reported in patients who have discontinued anti-hepatitis B therapy [including lamivudine tablets (HBV)]. Monitor hepatic function closely in these patients and, if appropriate, initiate anti-hepatitis B treatment. (5.1)
- Lamivudine tablets (HBV) contain a lower dose of the same active ingredient (lamivudine) as Epivir tablets and oral solution used to treat human immunodeficiency virus type 1 (HIV-1) infection. HIV-1 resistance may emerge in chronic hepatitis B patients with unrecognized or untreated HIV-1 infection because the lamivudine dosage in lamivudine tablets (HBV) is subtherapeutic and monotherapy is inappropriate for the treatment of HIV-1 infection. HIV counseling and testing should be offered to all patients before beginning treatment with lamivudine tablets (HBV) and periodically during treatment. (5.2)

1 INDICATIONS AND USAGE

- Lamivudine tablets (HBV) are a nucleoside analogue reverse transcriptase inhibitor indicated for the treatment of chronic hepatitis B virus (HBV) infection associated with evidence of hepatitis B viral replication and active liver inflammation. (1)

2 DOSAGE AND ADMINISTRATION

- Adults: 100 mg, once daily. (2.2)
- Pediatric Patients aged 2 to 17 years: 3 mg per kg once daily up to 100 mg once daily. Prescribe oral solution for pediatric patients requiring less than 100 mg daily. (2.3)
- Patients with Renal Impairment: Doses of lamivudine tablets (HBV) must be adjusted in accordance with renal function. (2.4)
- Lamivudine tablets (HBV) should not be used with other medications that contain lamivudine or emtricitabine. (2.5)

3 DOSAGE FORMS AND STRENGTHS

- Tablets: 100 mg (3)

4 CONTRAINDICATIONS

Lamivudine tablets (HBV) is contraindicated in patients with previous hypersensitivity reaction to lamivudine. (4)

5 WARNINGS AND PRECAUTIONS

- Emergence of Resistance-Associated HBV Substitutions: Consider a switch to an alternative regimen if serum HBV DNA remains detectable after 24 weeks of treatment. (2.6, 5.3)
- Lactic acidosis and severe hepatomegaly with steatosis, including fatal cases, have been reported with the use of nucleoside analogues. (5.4)

6 ADVERSE REACTIONS

The most common reported adverse reactions in those receiving lamivudine tablets (HBV) (incidence greater than or equal to 10% and reported at a rate greater than placebo) were ear, nose, and throat infections; sore throat; and diarrhea. (6.1)

To report SUSPECTED ADVERSE REACTIONS, contact Apotex Corp. at 1-800-706-5575 or FDA at 1-800-FDA-1088 or www.fda.gov/medwatch.

7 DRUG INTERACTIONS

Sorbitol: Coadministration of lamivudine and sorbitol may result in decreased lamivudine concentrations; when possible, avoid chronic coadministration. Consider more frequent monitoring of HBV viral load when chronic coadministration cannot be avoided. (7.2)

FULL PRESCRIBING INFORMATION

WARNING: EXACERBATIONS OF HEPATITIS B, AND RISK OF HIV-1 RESISTANCE IF LAMIVUDINE TABLETS (HBV) IS USED IN PATIENTS WITH UNRECOGNIZED OR UNTREATED HIV-1 INFECTION

Severe acute exacerbations of hepatitis B have been reported in patients who have discontinued anti-hepatitis B therapy [including lamivudine tablets (HBV)]. Hepatic function should be monitored closely with both clinical and laboratory follow-up for at least several months in patients who discontinue anti-hepatitis B therapy. If appropriate, initiation of anti-hepatitis B therapy may be warranted[ see Warnings and Precautions (5.1)]

Lamivudine tablets (HBV) is not approved for the treatment of human immunodeficiency virus type 1(HIV-1) infection because the lamivudine dosage in lamivudine tablets (HBV) is subtherapeutic and monotherapy is inappropriate for the treatment of HIV-1 infection. HIV-1 resistance may emerge in chronic hepatitis B-infected patients with unrecognized or untreated HIV-1 infection. HIV counseling and testing should be offered to all patients before beginning treatment with lamivudine tablets (HBV) and periodically during treatment [see Warnings and Precaution (5.1) ]

1 INDICATIONS AND USAGE

Lamivudine tablets (HBV) are indicated for the treatment of chronic hepatitis B virus (HBV) infection associated with evidence of hepatitis B viral replication and active liver inflammation [ see Clinical Studies (14.1, 14.2) ].

The following points should be considered when initiating therapy with lamivudine tablets (HBV):

- Due to high rates of resistance development in treated patients, initiation of treatment with lamivudine tablets (HBV) should only be considered when the use of an alternative antiviral agent with a higher genetic barrier to resistance is not available or appropriate.
- Lamivudine tablets (HBV) have not been evaluated in patients co-infected withhuman immunodeficiency virus(HIV), hepatitis C virus (HCV), or hepatitis delta virus.
- Lamivudine tablets (HBV) have not been evaluated in liver transplant recipients or in patients with chronic hepatitis B virus infection with decompensated liver disease.

2 DOSAGE AND ADMINISTRATION

2.1 HIV Counseling and Testing

HIV counseling and testing should be offered to all patients before beginning treatment with Lamivudine tablets (HBV) and periodically during treatment because of the risk of emergence of resistanthuman immunodeficiency virus type 1(HIV-1) and limitation of treatment options if lamivudine tablets (HBV) is prescribed to treat chronic hepatitis B infection in a patient who has unrecognized HIV-1 infection or acquires HIV-1 infection during treatment [ see Warnings and Precautions (5.2) ].

2.2 Recommended Dosage for Adult Patients

The recommended oral dosage of lamivudine tablets (HBV) is 100 mg once daily.

2.3 Recommended Dosage for Pediatric Patients

The recommended oral dosage of lamivudine tablets (HBV) for pediatric patients aged 2 to 17 years is 3 mg per kg once daily up to a maximum daily dosage of 100 mg. The oral solution formulation should be prescribed for patients requiring a dosage less than 100 mg or if unable to swallow tablets.

2.4 Patients with Renal Impairment

Dosage recommendations for adult patients with reduced renal function are provided in Table 1 [ see Clinical Pharmacology (12.3) ].

Table 1. Dosage of Lamivudine Tablets (HBV) in Adult Patients with Renal Impairment
Creatinine Clearance; (mL/min) | Recommended Dosage of Lamivudine Tablets (HBV)
≥50 | 100 mg once daily
30-49 | 100 mg first dose, then 50 mg once daily
15-29 | 100 mg first dose, then 25 mg once daily
5-14 | 35 mg first dose, then 15 mg once daily
<5 | 35 mg first dose, then 10 mg once daily

Following correction of the dosage for renal impairment, no additional dosage modification of lamivudine tablets (HBV) is required after routine (4-hour) hemodialysis or peritoneal dialysis [ see Clinical Pharmacology (12.3)] .

There are insufficient data to recommend a specific dosage of lamivudine tablets (HBV) in pediatric patients with renal impairment.

2.5 Important Administration Instructions

- Lamivudine tablets (HBV) may be administered with or without food.
- The tablets and oral solution may be used interchangeably [ see Clinical Pharmacology (12.3) ].
- The oral solution should be used for doses less than 100 mg.
- Lamivudine tablets (HBV) should not be used with other medications that contain lamivudine or medications that contain emtricitabine.

2.6 Assessing Patients during Treatment

Patients should be monitored regularly during treatment by a physician experienced in the management of chronic hepatitis B. During treatment, combinations of events such as return of persistently elevated ALT, increasing levels of HBV DNA over time after an initial decline below assay limit, progression of clinical signs or symptoms of hepatic disease, and/or worsening of hepatic necroinflammatory findings may be considered as potentially reflecting loss of therapeutic response. Such observations should be taken into consideration when determining the advisability of continuing therapy with lamivudine tablets (HBV).

The optimal duration of treatment, the durability of HBeAg seroconversions occurring during treatment, and the relationship between treatment response and long-term outcomes such as hepatocellular carcinoma or decompensated cirrhosis are not known.

3 DOSAGE FORMS AND STRENGTHS

- Lamivudine tablets (HBV): 100 mg, are orange-brown, capsule shaped, biconvex film-coated tablets engraved “APO” on one side, “LMV 100” on the other side.

4 CONTRAINDICATIONS

Lamivudine tablets (HBV) are contraindicated in patients with a previous hypersensitivity reaction to lamivudine.

5 WARNINGS AND PRECAUTIONS

5.1 Exacerbations of Hepatitis after Discontinuation of Treatment

Clinical and laboratory evidence of exacerbations of hepatitis have occurred after discontinuation of lamivudine. These exacerbations have been detected primarily by serum ALT elevations in addition to re-emergence of HBV DNA commonly observed after stopping treatment; see Table 4 for more information regarding frequency of posttreatment ALT elevations [ see Adverse Reactions (6.1) ]. Although most events appear to have been self-limited, fatalities have been reported in some cases. The causal relationship to discontinuation of lamivudine treatment is unknown. Patients should be closely monitored with both clinical and laboratory follow-up for at least several months after stopping treatment with lamivudine tablets (HBV). There is insufficient evidence to determine whether re-initiation of lamivudine tablets (HBV) alters the course of posttreatment exacerbations of hepatitis.

5.2 Risk of HIV-1 Resistance if Lamivudine Tablets (HBV) is Used in Patients with Unrecognized or Untreated HIV-1 Infection

Lamivudine tablets (HBV) contain a lower lamivudine dose than the lamivudine dose used to treat HIV-1 infection with Epivir tablets and oral solution or with lamivudine containing antiretroviral fixed-dose combination products.

Lamivudine tablets (HBV) is not appropriate for patients co-infected with HBV and HIV-1. If a patient with unrecognized or untreated HIV-1 infection is prescribed lamivudine tablets (HBV) for the treatment of HBV, rapid emergence of HIV-1 resistance is likely to result because of the subtherapeutic dose and the inappropriate use of monotherapy for HIV-1 treatment. HIV counseling and testing should be offered to all patients before beginning treatment with lamivudine tablets (HBV) and periodically during treatment because of the risk of rapid emergence of resistant HIV-1 and limitation of treatment options if lamivudine tablets (HBV) is prescribed to treat chronic hepatitis B in a patient who has unrecognized or untreated HIV-1 infection or who acquires HIV-1 infection during treatment.

5.3 Emergence of Resistance-Associated HBV Substitutions

In controlled clinical trials, YMDD-mutant HBV was detected in subjects with on–lamivudine tablets (HBV) re-appearance of HBV DNA after an initial decline below the assay limit [see Microbiology (12.4)]. Subjects treated with lamivudine tablets (HBV) (adults and children) with YMDD-mutant HBV at 52 weeks showed diminished treatment responses in comparison with subjects treated with lamivudine tablets (HBV) without evidence of YMDD substitutions, including the following: lower rates of HBeAg seroconversion and HBeAg loss (no greater than placebo recipients), more frequent return of positive HBV DNA, and more frequent ALT elevations. In the controlled trials, when subjects developed YMDD-mutant HBV, they had a rise in HBV DNA and ALT from their previous on-treatment levels. Progression of hepatitis B, including death, has been reported in some subjects with YMDD-mutant HBV, including subjects from the liver transplant setting and from other clinical trials. In order to reduce the risk of resistance in patients receiving monotherapy with lamivudine tablets (HBV), a switch to an alternative regimen should be considered if serum HBV DNA remains detectable after 24 weeks of treatment. Optimal therapy should be guided by resistance testing.

5.4 Lactic Acidosis and Severe Hepatomegaly with Steatosis

Lactic acidosis and severe hepatomegaly with steatosis, including fatal cases, have been reported with the use of nucleoside analogues, including lamivudine tablets (HBV). A majority of these cases have been in women. Female sex and obesity may be risk factors for the development of lactic acidosis and severe hepatomegaly with steatosis in patients treated with antiretroviral nucleoside analogues. Most of these reports have described patients receiving nucleoside analogues for treatment of HIV infection, but there have been reports of lactic acidosis in patients receiving lamivudine for hepatitis B. Treatment with lamivudine tablets (HBV) should be suspended in any patient who develops clinical or laboratory findings suggestive of lactic acidosis or pronounced hepatotoxicity which may include hepatomegaly and steatosis even in the absence of marked transaminase elevations.

6 ADVERSE REACTIONS

The following adverse reactions are discussed in other sections of the labeling:

- Exacerbations of hepatitis B after discontinuation of treatment [ see Warnings and Precautions (5.1) ].
- Risk of emergence of resistant HIV-1 infection [ see Warnings and Precautions (5.2) ].
- Risk of emergence of resistant HBV infection [ see Warnings and Precautions (5.3)].
- Lactic acidosis and severe hepatomegaly with steatosis [ see Warnings and Precautions (5.4) ].

6.1 Clinical Trials Experience

Because clinical trials are conducted under widely varying conditions, adverse reaction rates observed in the clinical trials of a drug cannot be directly compared with rates in the clinical trials of another drug and may not reflect the rates observed in clinical practice.

Clinical Trials Experience in Adult Subjects with Chronic HBV Infection

Clinical adverse reactions (regardless of investigator’s causality assessment) reported in greater than or equal to 10% of subjects who received lamivudine tablets (HBV) and reported at a rate greater than in subjects who received placebo are listed in Table 2.

Table 2. Clinical Adverse ReactionsaReported in Greater than or Equal to 10% of Subjects Who Received Lamivudine Tablets (HBV) for 52 to 68 Weeks and at an Incidence Greater than Placebo (Trials 1 to 3)
Adverse Event | Lamivudine Tablets (HBV); (n = 332) | Placebo; (n = 200)
Ear, Nose, and Throat
Ear, nose, and throat infections | 25% | 21%
Sore throat | 13% | 8%
Gastrointestinal
Diarrhea | 14% | 12%
aIncludes adverse events regardless of severity and causality assessment.

Specified laboratory abnormalities reported in subjects who received lamivudine tablets (HBV) and reported at a rate greater than in subjects who received placebo are listed in Table 3.

Table 3. Frequencies of Specified Laboratory Abnormalities Reported during Treatment at a Greater Frequency in Subjects Treated with Lamivudine Tablets (HBV) than with Placebo (Trials 1 to 3)a
Test; (Abnormal Level) | Subjects with Abnormality/Subjects with Observations
Test; (Abnormal Level) | Lamivudine Tabglets (HBV) | Placebo
Serum Lipase ≥2.5 x ULNb | 10% | 7%
Creatine Phosphokinase (CPK) ≥7 x baseline | 9% | 5%
Platelets <50,000/mm^3 | 4% | 3%
aIncludes subjects treated for 52 to 68 weeks.
bIncludes observations during and after treatment in the 2 placebo-controlled trials that collected this information.
ULN = Upper limit of normal.

In subjects followed for up to 16 weeks after discontinuation of treatment, posttreatment ALT elevations were observed more frequently in subjects who had received lamivudine tablets (HBV) than in subjects who had received placebo. A comparison of ALT elevations between Weeks 52 and 68 in subjects who discontinued lamivudine tablets (HBV) at Week 52 and subjects in the same trials who received placebo throughout the treatment course is shown in Table 4.

Table 4. Posttreatment ALT Elevations with No-Active-Treatment Follow-up (Trials 1 and 3)
Abnormal Value | Subjects with ALT Elevation/ Subjects with Observationsa
Abnormal Value | Lamivudine Tablets (HBV)b | Placebob
ALT ≥2 x baseline value | 27% | 19%
ALT ≥3 x baseline valuec | 21% | 8%
ALT ≥2 x baseline value and absolute ALT >500 IU/L | 15% | 7%
ALT ≥2 x baseline value; and bilirubin >2 x ULN and ≥2 x baseline value | 0.7% | 0.9%
aEach subject may be represented in one or more category.
b During treatment phase.
cComparable to a Grade 3 toxicity in accordance with modified WHO criteria.
ULN = Upper limit of normal.

Clinical Trials Experience in Pediatric Subjects with Chronic HBV Infection

Most commonly observed adverse reactions in the pediatric trials were similar to those in adult trials. Posttreatment transaminase elevations were observed in some subjects followed after cessation of lamivudine tablets (HBV).

6.2 Postmarketing Experience

The following adverse reactions have been identified during post-approval use of lamivudine tablets (HBV). Because these reactions are reported voluntarily from a population of unknown size, it is not always possible to reliably estimate their frequency or establish a causal relationship to drug exposure. These reactions have been chosen for inclusion due to a combination of their seriousness, frequency of reporting, or potential causal connection to lamivudine.

Blood and Lymphatic
Anemia (including pure red cell aplasia and severe anemias progressing on therapy), lymphadenopathy, splenomegaly, thrombocytopenia.

Digestive
Stomatitis.

Endocrine and Metabolic
Hyperglycemia.

General
Weakness.

Hepatic and Pancreatic
Lactic acidosis and steatosis [see Warnings and Precautions (5.4) ], posttreatment exacerbations of hepatitis [see Warnings and Precautions (5.1)] , pancreatitis.

Hypersensitivity
Anaphylaxis, urticaria.

Musculoskeletal
Cramps, rhabdomyolysis.

Nervous
Paresthesia, peripheral neuropathy.

Respiratory
Abnormal breath sounds/wheezing.

Skin
Alopecia, pruritus, rash.

7 DRUG INTERACTIONS

7.1 Drugs Inhibiting Organic Cation Transporters

Lamivudine is predominantly eliminated in the urine by active organic cationic secretion. The possibility of interactions with other drugs administered concurrently should be considered, particularly when their main route of elimination is active renal secretion via the organic cationic transport system (e.g., trimethoprim) [see Clinical Pharmacology (12.3)] . No data are available regarding interactions with other drugs that have renal clearance mechanisms similar to that of lamivudine.

7.2 Sorbitol

Coadministration of single doses of lamivudine and sorbitol resulted in a sorbitol dose-dependent reduction in lamivudine exposures. When possible, avoid use of sorbitol-containing medicines with lamivudine [see Clinical Pharmacology (12.3)] . Consider more frequent monitoring of HBV viral load when chronic coadministration cannot be avoided.

8 USE IN SPECIFIC POPULATIONS

8.1 Pregnancy

Pregnancy Exposure Registry

There is a pregnancy exposure registry that monitors pregnancy outcomes in women exposed to lamivudine during pregnancy. Healthcare providers are encouraged to register patients by calling the Antiretroviral Pregnancy Registry (APR) at 1-800-258-4263.

Risk Summary

Available data from the APR show no substantial difference in the risk of overall major birth defects for lamivudine compared with the background rate for major birth defects of 2.7% reported in the U.S. reference population of the Metropolitan Atlanta Congenital Defects Program (MACDP). The APR uses the MACDP as a U.S. reference population for birth defects in the general population. The MACDP evaluates women and infants from a limited geographic area and does not include outcomes for births that occur at less than 20 weeks’ gestation. Of over 12,900 women exposed to lamivudine in the APR, less than 2% were HBV mono-infected. The majority of women exposed to lamivudine in the APR were HIV-1-infected and were treated with higher doses of lamivudine compared with HBV mono-infected women. In addition to lamivudine, HIV-1-infected women were also treated with other concomitant medications for HIV-1 infection [see Data]. The estimated rate of miscarriage for women exposed to lamivudine in the indicated population is unknown. The estimated background rate of miscarriage in clinically recognized pregnancies in the U.S. general population is 15% to 20%.

Oral administration of lamivudine to pregnant rabbits during organogenesis resulted in embryolethality at systemic exposure (AUC) similar to the recommended clinical dose; however, no adverse developmental effects were observed with oral administration of lamivudine to pregnant rats during organogenesis at plasma concentrations (Cmax) 60 times the recommended clinical dose [see Data].

Data

Human Data

Based on prospective reports from the APR of over 12,900 exposures to lamivudine during pregnancy resulting in live births (including over 5,400 exposed in the first trimester and over 7,500 exposed in the second/third trimester), there was no difference between the overall risk of birth defects with lamivudine compared with the background birth defect rate of 2.7% observed in the U.S. reference population of the MACDP.The prevalence of birth defects in live births was 3.1% (95% CI: 2.7% to 3.6%) following first trimester exposure to lamivudine-containing regimens and 2.9% (95% CI: 2.5% to 3.3%) following second/third trimester exposure to lamivudine-containing regimens.

The pharmacokinetics of lamivudine in patients with HBV or HIV-1 infection and in healthy volunteers are similar at similar doses. Lamivudine pharmacokinetics were studied in pregnant women with HIV-1 infection during 2 clinical trials conducted in South Africa. The trials assessed pharmacokinetics in 16 women at 36 weeks gestation using 150 mg lamivudine twice daily (3 times the recommended daily dosage for HBV) with zidovudine, 10 women at 38 weeks gestation using 150 mg lamivudine twice daily (3 times the recommended daily dosage for HBV) with zidovudine, and 10 women at 38 weeks gestation using lamivudine 300 mg twice daily (6 times the recommended daily dosage for HBV) without other antiretrovirals. Lamivudine concentrations were generally similar in maternal, neonatal, and umbilical cord serum samples.

In a subset of subjects, amniotic fluid specimens were collected following natural rupture of membranes and confirmed that lamivudine crosses the placenta in humans. Based on limited data at delivery, median (range) amniotic fluid concentrations of lamivudine were 3.9- (1.2- to 12.8-) fold greater compared with paired maternal serum concentrations (n = 8).

Animal Data
Lamivudine was administered orally to pregnant rats (at 90, 600, and 4,000 mg per kg per day) and rabbits (at 90, 300, and 1,000 mg per kg per day and at 15, 40, and 90 mg per kg per day) during organogenesis (on Gestation Days 7 through 16 [rat] and 8 through 20 [rabbit]). No evidence of fetal malformations due to lamivudine was observed in rats and rabbits at doses producing plasma concentrations (Cmax) approximately 53 or more times higher than human exposure at the recommended daily dose. Evidence of early embryolethality in the absence of maternal toxicity was seen in the rabbit at systemic exposures (AUC) similar to those observed in humans, but there was no indication of this effect in the rat at plasma concentrations (Cmax) 60 times higher than human exposure at the recommended daily dose. Studies in pregnant rats showed that lamivudine is transferred to the fetus through the placenta. In the fertility/pre- and postnatal development study in rats, lamivudine was administered orally at doses of 180, 900, and 4,000 mg per kg per day (from prior to mating through postnatal Day 20). In the study, development of the offspring, including fertility and reproductive performance, was not affected by maternal administration of lamivudine at plasma concentrations (Cmax) 104 times higher than human exposure.

8.2 Lactation

Risk Summary

Lamivudine is present in human milk. There is no information available regarding lamivudine concentrations in milk from lactating women receiving lamivudine for treatment of HBV infection. However, in lactating women with HIV-1 infection being treated with lamivudine at 3 or 6 times the recommended daily dose for HBV, lamivudine concentrations in milk were similar to those observed in serum [see Data]. The lamivudine dose received by a breastfed infant of a mother being treated for HIV-1 infection was estimated to be approximately 6% of the recommended daily lamivudine dose for HBV in children over 2 years of age.

There is no information available regarding the effects of the drug on the breastfed infant or on milk production.

The developmental and health benefits of breastfeeding should be considered along with the mother’s clinical need for lamivudine tablets (HBV) and any potential adverse effects on the breastfed infant from lamivudine or from the underlying maternal condition.

Data

In mothers with HIV receiving lamivudine monotherapy (300 mg twice daily [6 times the recommended daily dosage for HBV]) or combination therapy (150 mg lamivudine twice daily [3 times the recommended daily dosage for HBV] with 300 mg zidovudine twice daily), the median breast milk to plasma lamivudine concentration ratio was 0.6 to 3.3, and the estimated infant daily dose was approximately 6% of the recommended 3-mg-per-kg daily lamivudine dose for treatment of HBV in children over 2 years of age. In breastfed infants of mothers with HIV-1 infection receiving lamivudine therapy, the blood concentrations of lamivudine decreased after delivery and were undetectable at 6 months despite constant milk concentrations. This is consistent with increased lamivudine renal clearance in the first 6 months of life.

8.4 Pediatric Use

Lamivudine tablets (HBV) is indicated for the treatment of chronic hepatitis B virus infection in pediatric patients aged 2 to 17 years [ see Indications and Usage (1) , Clinical Pharmacology (12.3) , Clinical Studies (14.2) ]. The safety and efficacy of lamivudine tablets (HBV) in pediatric patients younger than 2 years have not been established.

8.5 Geriatric Use

Clinical trials of lamivudine tablets (HBV) did not include sufficient numbers of subjects aged 65 and over to determine whether they respond differently from younger subjects. In general, caution should be exercised in the administration of lamivudine tablets (HBV) in elderly patients reflecting the greater frequency of decreased hepatic, renal, or cardiac function, and of concomitant disease or other drug therapy [see Dosage and Administration (2.4), Clinical Pharmacology (12.3)] .

8.6 Patients with Impaired Renal Function

Reduction of the dosage of lamivudine tablets (HBV) is recommended for patients with impaired renal function [ see Dosage and Administration (2.4) , Clinical Pharmacology (12.3) ].

8.7 Patients with Impaired Liver Function

No dose adjustment for lamivudine is required for patients with impaired hepatic function.

10 OVERDOSAGE

There is no known specific treatment for overdose with lamivudine tablets (HBV). If overdose occurs, the patient should be monitored and standard supportive treatment applied, as required. Because a negligible amount of lamivudine was removed via (4-hour) hemodialysis, continuous ambulatory peritoneal dialysis, and automated peritoneal dialysis, it is not known if continuous hemodialysis would provide clinical benefit in a lamivudine overdose event.

11 DESCRIPTION

Lamivudine tablets (HBV) is a synthetic nucleoside analogue with activity against HBV. The drug substance used in lamivudine tablets (HBV) is lamivudine in the form of lamivudine methanol solvate. The chemical name of lamivudine methanol solvate is (2R,cis)-4-amino-1-(2-hydroxymethyl-1,3-oxathiolan-5-yl))2(1H)-pyrimidinone methanol solvate. It has a molecular formula of C8H11N3O3S• O.2 CH4O C8H11N3O3S and a molecular weight of 235.66 g/mol. It has the following structural formula:

Lamivudine is a white to off-white powder. It is highly soluble in water.

Lamivudine tablets (HBV) are for oral administration. Each tablet contains lamivudine methanol solvate equivalent to 100 mg of lamivudine and the inactive ingredients anhydrous lactose, colloidal silicon dioxide, crospovidone, ferric oxide red, ferric oxide yellow, hydroxypropyl cellulose, hypromellose, magnesium stearate, polyethylene glycol and titanium dioxide.

Meets with USP dissolution test # 2

12 CLINICAL PHARMACOLOGY

12.1 Mechanism of Action

Lamivudine is an antiviral agent with activity against HBV [see Microbiology (12.4) ].

12.3 Pharmacokinetics

Pharmacokinetics in Adults

The pharmacokinetic properties of lamivudine have been studied as single and multiple oral doses ranging from 5 mg to 600 mg per day administered to HBV-infected subjects.

Absorption and Bioavailability:

Following single oral doses of 100 mg, the peak serum lamivudine concentration (Cmax) in HBV-infected patients (steady state) and healthy subjects (single dose) was 1.28 ± 0.56 mcg per mL and 1.05 ± 0.32 mcg per mL (mean ± SD), respectively, which occurred between 0.5 and 2 hours after administration. The area under the plasma concentration versus time curve (AUC[0-24 h]) following 100-mg lamivudine oral single and repeated daily doses to steady state was 4.3 ± 1.4 (mean ± SD) and 4.7 ± 1.7 mcg•hour per mL, respectively. The relative bioavailability of the tablet and oral solution were demonstrated in healthy subjects. Although the solution demonstrated a slightly higher peak serum concentration (Cmax), there was no significant difference in systemic exposure (AUC) between the oral solution and the tablet. Therefore, the oral solution and the tablet may be used interchangeably.

After oral administration of lamivudine once daily to HBV-infected adults, the AUC and Cmax increased in proportion to dose over the range from 5 mg to 600 mg once daily.

Absolute bioavailability in 12 adult subjects was 86% ± 16% (mean ± SD) for the 150-mg tablet and 87% ± 13% for the 10-mg per mL oral solution.

Effects of Food on Oral Absorption:

Lamivudine tablets (HBV) may be administered with or without food. The 100-mg tablet was administered orally to 24 healthy subjects on 2 occasions, once in the fasted state and once with food (standard meal: 967 kcal; 67 grams fat, 33 grams protein, 58 grams carbohydrate). There was no significant difference in systemic exposure (AUC) in the fed and fasted states.

Distribution:

The apparent volume of distribution after IV administration of lamivudine to 20 HIV-1-infected subjects was 1.3 ± 0.4 L per kg, suggesting that lamivudine distributes into extravascular spaces. Volume of distribution was independent of dose and did not correlate with body weight.

Binding of lamivudine to human plasma proteins is less than 36%. In vitrostudies showed that over the concentration range of 0.1 to 100 mcg per mL, the amount of lamivudine associated with erythrocytes ranged from 53% to 57% and was independent of concentration.

Metabolism:

Metabolism of lamivudine is a minor route of elimination. In humans, the only known metabolite of lamivudine is the trans-sulfoxide metabolite (approximately 5% of an oral dose after 12 hours). Serum concentrations of this metabolite have not been determined. Lamivudine is not significantly metabolized by cytochrome P450 enzymes.

Elimination:

The majority of lamivudine is eliminated unchanged in urine by active organic cationic secretion. In 9 healthy subjects given a single 300-mg oral dose of lamivudine, renal clearance was 199.7 ± 56.9 mL per min (mean ± SD). In 20 HIV-1-infected subjects given a single IV dose, renal clearance was 280.4 ± 75.2 mL per min (mean ± SD), representing 71% ± 16% (mean ± SD) of total clearance of lamivudine.

In most single-dose trials with plasma sampling for up to 48 or 72 hours after dosing, the observed mean elimination half-life (t½) ranged from 13 to 19 hours. In HIV-1-infected subjects, total clearance was 398.5 ± 69.1 mL per min (mean ± SD). Oral clearance and elimination half-life were independent of dose and body weight over an oral dosing range of 0.25 to 10 mg per kg.

Specific Populations

Patients with Renal Impairment

The pharmacokinetic properties of lamivudine have been determined in healthy adults and in adults with impaired renal function, with and without hemodialysis (Table 5).

Table 5. Pharmacokinetic Parameters (Mean ± SD) Dose-Normalized to a Single 100-mg Oral Dose of Lamivudine in Adults with Varying Degrees of Renal Function

Parameter | Creatinine Clearance Criterion (Number of Subjects)
Parameter | ≥ 80 mL/min (n = 9) | 20-59 mL/min (n = 8) | <20 mL/min (n = 6)
Creatinine clearance (mL/min) | 97 (range 82-117) | 39 (range 25-49) | 15 (range 13-19)
Cmax (mcg/mL) | 1.31 ± 0.35 | 1.85 ± 0.40 | 1.55 ± 0.31
AUC (mcg•h/mL) | 5.28 ± 1.01 | 14.67 ± 3.74 | 27.33 ± 6.56
Cl/F (mL/min) | 326.4 ± 63.8 | 120.1 ± 29.5 | 64.5 ± 18.3

Tmax was not significantly affected by renal function. Based on these observations, it is recommended that the dosage of lamivudine be modified in patients with renal impairment [see Dosage and Administration (2.4)] .

Hemodialysis increases lamivudine clearance from a mean of 64 to 88 mL per min; however, the length of time of hemodialysis (4 hours) was insufficient to significantly alter mean lamivudine exposure after a single-dose administration. Continuous ambulatory peritoneal dialysis and automated peritoneal dialysis have negligible effects on lamivudine clearance. Therefore, it is recommended, following correction of dose for creatinine clearance, that no additional dose modification be made after routine hemodialysis or peritoneal dialysis.

The effects of renal impairment on lamivudine pharmacokinetics in pediatric patients with chronic hepatitis B is not known.

Patients with Hepatic Impairment

The pharmacokinetic properties of lamivudine in adults with hepatic impairment are shown in Table 6. Subjects were stratified by severity of hepatic impairment.

Table 6. Pharmacokinetic Parameters (Mean ± SD) Dose-Normalized to a Single 100-mg Dose of Lamivudine in Adults with Normal or Impaired Hepatic Function

Parameter | Normal (n = 8) | Impairmenta
Parameter | Normal (n = 8) | Moderate (n = 8) | Severe (n = 8)
Cmax (mcg/mL) | 0.92 ± 0.31 | 1.06 ± 0.58 | 1.08 ± 0.27
AUC (mcg•h/mL) | 3.96 ± 0.58 | 3.97 ± 1.36 | 4.30 ± 0.63
Tmax (h) | 1.3 ± 0.8 | 1.4 ± 0.8 | 1.4 ± 1.2
Cl/F (mL/min) | 424.7 ± 61.9 | 456.9 ± 129.8 | 395.2 ± 51.8
Clr (mL/min) | 279.2 ± 79.2 | 323.5 ± 100.9 | 216.1 ± 58.0

a Hepatic impairment assessed by aminopyrine breath test.

Pharmacokinetic parameters were not altered by diminishing hepatic impairment. Safety and efficacy of lamivudine tablets (HBV) have not been established in the presence of decompensated liver disease [see Indications and Usage (1)] .

Patients Post-Hepatic Transplant

Fourteen HBV-infected adult subjects received liver transplant following lamivudine therapy and completed pharmacokinetic assessments at enrollment, 2 weeks after 100-mg once-daily dosing (pre-transplant), and 3 months following transplant; there were no significant differences in pharmacokinetic parameters. The overall exposure of lamivudine is primarily affected by renal impairment; consequently, transplant patients with renal impairment had generally higher exposure than patients with normal renal function. Safety and efficacy of lamivudine tablets (HBV) have not been established in this population [see Indications and Usage (1)] .

Pregnant Women

The pharmacokinetics of lamivudine in patients with HBV or HIV-1 infection and in healthy volunteers were similar at similar doses. Lamivudine pharmacokinetics were studied in 36 pregnant women with HIV during 2 clinical trials conducted in South Africa (3 to 6 times the recommended daily dosage for HBV). Lamivudine pharmacokinetics in pregnant women were similar to those seen in non-pregnant adults and in postpartum women. Lamivudine concentrations were generally similar in maternal, neonatal, and umbilical cord serum samples.

Pediatric Patients

Lamivudine pharmacokinetics were evaluated in a 28-day dose-ranging trial in 53 pediatric subjects with chronic hepatitis B. Subjects aged 2 to 12 years were randomized to receive lamivudine 0.35 mg per kg twice daily, 3 mg per kg once daily, 1.5 mg per kg twice daily, or 4 mg per kg twice daily. Subjects aged 13 to 17 years received lamivudine 100 mg once daily. Lamivudine Tmax was 0.5 to 1 hour. In general, both Cmax and exposure (AUC) showed dose proportionality in the dosing range studied. Weight-corrected oral clearance was highest at age 2 and declined from 2 to 12 years, where values were then similar to those seen in adults. A dose of 3 mg per kg given once daily produced a steady-state lamivudine AUC (mean 5,953 ng•hour per mL ± 1,562 SD) similar to that associated with a dose of 100 mg per day in adults.

Geriatric Patients

The pharmacokinetics of lamivudine after administration of lamivudine tablets (HBV) to subjects over 65 years have not been studied [see Use in Specific Populations (8.5)] .

Male and Female Patients

There are no significant or clinically relevant gender differences in lamivudine pharmacokinetics.

Racial Groups

There are no significant or clinically relevant racial differences in lamivudine pharmacokinetics.

Drug Interaction Studies

Effect of Lamivudine on the Pharmacokinetics of Other Agents

Based on in vitrostudy results, lamivudine at therapeutic drug exposures is not expected to affect the pharmacokinetics of drugs that are substrates of the following transporters: organic anion transporter polypeptide 1B1/3 (OATP1B1/3), breast cancer resistance protein (BCRP), P-glycoprotein (P-gp), multidrug and toxin extrusion protein 1 (MATE1), MATE2-K, organic cation transporter 1 (OCT1), OCT2 or OCT3.

Effect of Other Agents on the Pharmacokinetics of Lamivudine

Lamivudine is a substrate of MATE1, MATE2-K, and OCT2 in vitro. Trimethoprim (an inhibitor of these drug transporters) has been shown to increase lamivudine plasma concentrations. This interaction is not considered clinically significant, and no dose adjustment of lamivudine is needed.

Lamivudine is a substrate of P-gp and BCRP; however, considering its absolute bioavailability (87%), it is unlikely that these transporters play a significant role in the absorption of lamivudine. Therefore, coadministration of drugs that are inhibitors of these efflux transporters is unlikely to affect the disposition and elimination of lamivudine.

Interferon Alfa

There was no significant pharmacokinetic interaction between lamivudine and interferon alfa in a trial of 19 healthy male subjects.

Ribavirin

In vitrodata indicate ribavirin reduces phosphorylation of lamivudine, stavudine, and zidovudine. However, no pharmacokinetic (e.g., plasma concentrations or intracellular triphosphorylated active metabolite concentrations) or pharmacodynamic (e.g., loss of HIV-1/HCV virologic suppression) interaction was observed when ribavirin and lamivudine (n = 18), stavudine (n = 10), or zidovudine (n = 6) were coadministered as part of a multi-drug regimen to HIV-1/HCV co-infected subjects.

Sorbitol (Excipient)

Lamivudine and sorbitol solutions were coadministered to 16 healthy adult subjects in an open-label, randomized sequence, 4-period, crossover trial. Each subject received a single 300-mg dose of lamivudine oral solution alone or coadministered with a single dose of 3.2 grams, 10.2 grams, or 13.4 grams of sorbitol in solution. Coadministration of lamivudine with sorbitol resulted in dose-dependent decreases of 20%, 39%, and 44% in the AUC(0-24), 14%, 32%, and 36% in the AUC(∞), and 28%, 52%, and 55% in the Cmaxof lamivudine.

Trimethoprim/Sulfamethoxazole

Lamivudine and trimethoprim/sulfamethoxazole (TMP/SMX) were coadministered to 14 HIV-1-positive subjects in a single-center, open-label, randomized, crossover trial. Each subject received treatment with a single 300-mg dose of lamivudine and TMP 160 mg/SMX 800 mg once a day for 5 days with concomitant administration of lamivudine 300 mg with the fifth dose in a crossover design. Coadministration of TMP/SMX with lamivudine resulted in an increase of 43% ± 23% (mean ± SD) in lamivudine AUC∞, a decrease of 29% ± 13% in lamivudine oral clearance, and a decrease of 30% ± 36% in lamivudine renal clearance. The pharmacokinetic properties of TMP and SMX were not altered by coadministration with lamivudine.

Zidovudine

No clinically significant alterations in lamivudine or zidovudine pharmacokinetics were observed in 12 asymptomatic HIV-1-infected adult subjects given a single dose of zidovudine (200 mg) in combination with multiple doses of lamivudine (300 mg every 12 hours).

12.4 Microbiology

Mechanism of Action

Lamivudine is a synthetic nucleoside analogue. Intracellularly, lamivudine is phosphorylated to its active 5′-triphosphate metabolite, lamivudine triphosphate (3TC-TP). The principal mode of action of 3TC-TP is inhibition of the RNA- and DNA-dependent polymerase activities of HBV reverse transcriptase (rt) via DNA chain termination after incorporation of the nucleotide analogue.

Antiviral Activity

Activity of lamivudine against HBV in cell culture was assessed in HBV DNA-transfected 2.2.15 cells, HB611 cells, and infected human primary hepatocytes. EC50 values (the concentration of drug needed to reduce the level of extracellular HBV DNA by 50%) varied from 0.01 microM (2.3 ng per mL) to 5.6 microM (1,288 ng per mL) depending upon the duration of exposure of cells to lamivudine, the cell model system, and the protocol used. See the prescribing information for lamivudine tablets regarding activity of lamivudine against HIV. The anti-HBV activity of lamivudine in combination with adefovir or tenofovir in cell culture was not antagonistic.

Resistance

Lamivudine-resistant isolates have been identified in subjects with virologic breakthrough. Lamivudine-resistant HBV isolates develop rtM204V/I substitutions in the YMDD motif of the catalytic domain of the viral reverse transcriptase. rtM204V/I substitutions are frequently accompanied by other substitutions (rtV173L, rtL180M) which enhance the level of lamivudine resistance or act as compensatory substitutions improving replication efficiency. Other substitutions reported in lamivudine-resistant HBV isolates include rtH55R, rtL80I/V, rtV173M, rtA181T/V, rtT184S, rtF219Y, rtL229F/M/V/W, and rtQ267H.

In 4 controlled clinical trials evaluating lamivudine tablets (HBV) in adults with HBeAg-positive chronic hepatitis B virus infection (CHB), YMDD-mutant HBV was detected in 81 of 335 subjects receiving lamivudine tablets (HBV) once daily for 52 weeks. The prevalence of YMDD substitutions was less than 10% in each of these trials for subjects studied at 24 weeks and increased to an average of 24% (range in 4 trials: 16% to 32%) at 52 weeks. A similar prevalence of YMDD substitutions has been reported in large controlled Phase 3 clinical trials utilizing lamivudine tablets (HBV) as a comparator arm in adults with HBeAg-positive CHB for 48 weeks (range in 4 trials: 11% to 27%) and in adults with HBeAg-negative CHB for 48 weeks (range in 3 clinical trials: 6% to 18%).

Long-term follow up in subjects who continued 100 mg per day of lamivudine tablets (HBV) demonstrated that the prevalence of YMDD substitutions further increased from 23% (211 of 998) in Year 1, to 46% (368 of 796), 55% (378 of 688), 71% (421 of 592), and 65% (103 of 159) in Years 2, 3, 4, and 5, respectively.

In a controlled trial, treatment-naive subjects with HBeAg-positive CHB were treated with lamivudine tablets (HBV) or lamivudine tablets (HBV) plus adefovir dipivoxil combination therapy. Following 104 weeks of therapy, YMDD-mutant HBV was detected in 7 of 40 (18%) subjects receiving combination therapy compared with 15 of 35 (43%) subjects receiving therapy with only lamivudine tablets (HBV). In 2 controlled clinical trials, treatment-naive subjects who received 48 weeks of therapy with lamivudine tablets (HBV) in combination with pegylated interferon developed YMDD substitutions less frequently than subjects treated with lamivudine tablets (HBV) alone (1 of 173 [1%] versus 32 of 179 [18%] in HBeAg-negative subjects; 9 of 256 [4%] versus 69 of 254 [27%] in HBeAgpositive subjects).

Several clinical studies have evaluated alternative regimens in subjects who failed lamivudine tablets (HBV) due to development of lamivudine resistance. These studies demonstrated a higher rate of viral suppression and decreased development of viral resistance compared with continuation of monotherapy with lamivudine tablets (HBV).

Pediatric Subjects

In a controlled trial in pediatric subjects, YMDD-mutant HBV was detected in 31 of 166 (19%) subjects receiving lamivudine tablets (HBV) for 52 weeks. For a subgroup that remained on therapy with lamivudine tablets (HBV) in a follow-up trial, YMDD substitutions increased from 24% (29 of 121) at 12 months to 59% (68 of 115) at 24 months and 64% (66 of 103) at 36 months of treatment with lamivudine tablets (HBV).

Cross-Resistance

HBV containing lamivudine resistance-associated substitutions (rtL180M, rtM204I, rtM204V, rtL180M and rtM204V, rtV173L and rtL180M and rtM204V) retain susceptibility to adefovir dipivoxil but have reduced susceptibility to entecavir (greater than 30-fold) and telbivudine (greater than 100-fold). The lamivudine resistance-associated substitution rtA181T results in diminished response to adefovir and telbivudine. Similarly, HBV with entecavir resistance-associated substitutions (rtI169T and rtM250V, rtT184G and rtS202I) have greater than 1,000-fold reductions in susceptibility to lamivudine.

13 NONCLINICAL TOXICOLOGY

13.1 Carcinogenesis, Mutagenesis, Impairment of Fertility

Carcinogenesis

Long-term carcinogenicity studies with lamivudine in mice and rats showed no evidence of carcinogenic potential at exposures up to 34 times (mice), and 113 and 187 times (male and female rats, respectively) those observed in humans at the recommended therapeutic dose for chronic hepatitis B.

Mutagenesis

Lamivudine was mutagenic in an L5178Y mouse lymphoma assay and clastogenic in a cytogenetic assay using cultured human lymphocytes. Lamivudine was not mutagenic in a microbial mutagenicity assay, in an in vitrocell transformation assay, in a rat micronucleus test, in a rat bone marrow cytogenetic assay, and in an assay for unscheduled DNA synthesis in rat liver.

Impairment of Fertility

Lamivudine did not affect male or female fertility in rats at oral doses up to 4,000 mg per kg per day, associated with concentrations approximately 70 times (male) or 104 times (females) higher than the concentrations (Cmax) in humans at the dose of 100 mg [see Use in Specific Populations (8.1)] .

14 CLINICAL STUDIES

14.1 Adult Subjects

The safety and efficacy of lamivudine tablets (HBV) once daily versus placebo were evaluated in 3 controlled trials in subjects with compensated chronic hepatitis B virus infection. All subjects were aged 16 years or older and had chronic hepatitis B virus infection (serum HBsAg-positive for at least 6 months) accompanied by evidence of HBV replication (serum HBeAg-positive and positive for serum HBV DNA) and persistently elevated ALT levels and/or chronic inflammation on liver biopsy compatible with a diagnosis of chronic viral hepatitis. The results of these trials are summarized below.

- Trial 1 was a randomized, double-blind trial of lamivudine tablets (HBV) once daily versus placebo for 52 weeks followed by a 16-week no-treatment period in 141 treatment-naive U.S subjects.
- Trial 2 was a randomized, double-blind, 3-arm trial that compared lamivudine tablets (HBV) 25 mg once daily versus lamivudine tablets (HBV) once daily versus placebo for 52 weeks in 358 Asian subjects.
- Trial 3 was a randomized, partially-blind trial conducted primarily in North America and Europe in 238 subjects who had ongoing evidence of active chronic hepatitis B despite previous treatment with interferon alfa. The trial compared lamivudine 100 mg once daily for 52 weeks, followed by either lamivudine tablets (HBV) or matching placebo once daily for 16 weeks (Arm 1), versus placebo once daily for 68 weeks (Arm 2).
  Principal endpoint comparisons for the histologic and serologic outcomes in subjects receiving lamivudine tablets (HBV) (100 mg daily) or placebo in these trials are shown in the following tables.

Table 7. Histologic Response at Week 52 among Adult Subjects Receiving Lamivudine Tablets (HBV) 100 mg Once Daily or Placebo
Assessment | Trial 1 |  | Trial 2 |  | Trial 3
Assessment | Lamivudine Tablets (HBV) 100 mg (n = 62) | Placebo; (n = 63) | Lamivudine Tablets (HBV) 100 mg (n = 131) | Placebo; (n = 68) | Lamivudine Tablets (HBV) 100 mg (n = 110) | Placebo; (n = 54)
Improvementa | 55% | 25% | 56% | 26% | 56% | 26%
No Improvement | 27% | 59% | 36% | 62% | 25% | 54%
Missing Data | 18% | 16% | 8% | 12% | 19% | 20%
aImprovement was defined as a greater than or equal to 2-point decrease in the Knodell Histologic Activity Index (HAI) at Week 52 compared with pretreatment HAI. Subjects with missing data at baseline were excluded.

Table 8. HBeAg Seroconvertersaat Week 52 among Adult Subjects Receiving Lamivudine Tablets (HBV) 100 mg Once Daily or Placebo
Seroconversion | Trial 1 |  | Trial 2 |  | Trial 3
Seroconversion | Lamivudine Tablets (HBV) 100 mg; (n = 63) | Placebo; (n = 69) | Lamivudine Tablets (HBV) 100 mg; (n = 140) | Placebo; (n = 70) | Lamivudine Tablets (HBV) 100 mg; (n = 108) | Placebo; (n = 53)
Seroconverters | 17% | 6% | 16% | 4% | 15% | 13%
aThree-component seroconversion was defined as Week 52 values showing loss of HBeAg, gain of HBeAb, and reduction of HBV DNA to below the solution-hybridization assay limit. Subjects with negative baseline HBeAg or HBV DNA assay were excluded from the analysis.

Normalization of serum ALT levels was more frequent with treatment of lamivudine tablets (HBV) compared with placebo in Trials 1, 2, and 3.

The majority of subjects treated with lamivudine tablets (HBV) showed a decrease of HBV DNA to below the assay limit early in the course of therapy. However, reappearance of assay-detectable HBV DNA during treatment with lamivudine tablets (HBV) was observed in approximately one-third of subjects after this initial response.

14.2 Pediatric Subjects

The safety and efficacy of lamivudine tablets (HBV) were evaluated in a double-blind clinical trial in 286 subjects aged 2 to 17 years, who were randomized (2:1) to receive 52 weeks of lamivudine tablets (HBV) (3 mg per kg once daily to a maximum of 100 mg once daily) or placebo. All subjects had compensated chronic hepatitis B accompanied by evidence of hepatitis B virus replication (positive serum HBeAg and positive for serum HBV DNA by a research branched-chain DNA assay) and persistently elevated serum ALT levels. The combination of loss of HBeAg and reduction of HBV DNA to below the assay limit of the research assay, evaluated at Week 52, was observed in 23% of subjects treated with lamivudine tablets (HBV) and 13% of placebo-treated subjects. Normalization of serum ALT was achieved and maintained to Week 52 more frequently in subjects treated with lamivudine compared with placebo (55% versus 13%). As in the adult controlled trials, most subjects treated with lamivudine tablets (HBV) had decreases in HBV DNA below the assay limit early in treatment, but about one-third of subjects with this initial response had reappearance of assay-detectable HBV DNA during treatment. Adolescents (aged 13 to 17 years) showed less evidence of treatment effect than younger pediatric subjects.

16 HOW SUPPLIED/STORAGE AND HANDLING

Lamivudine tablets (HBV), 100 mg, are orange-brown, capsule shaped, biconvex film-coated tablets engraved “APO” on one side, “LMV 100” on the other side.

Bottles of 60 tablets (NDC 51407-866-60) with child-resistant closures.

Store at 20ºC to 25ºC (68ºF to 77ºF); excursions permitted from 15ºC to 30ºC (59ºF to 86ºF) [see USP Controlled Room Temperature].

17 PATIENT COUNSELING INFORMATION

Advise the patient to read the FDA-approved patient labeling (Patient Information).

Severe Acute Exacerbation of Hepatitis after Discontinuation of Treatment

Inform patients that discontinuation of anti-hepatitis B therapy, including lamivudine tablets (HBV), may result in severe acute exacerbations of hepatitis B including decompensation of liver disease. Advise patients not to discontinue lamivudine tablets (HBV) without first informing their healthcare provider [see Warnings and Precautions (5.1)] .

Risk of Development of HIV-1 Resistance in Patients with HIV-1 Co-infection

Counsel patients on the importance of testing for HIV to avoid inappropriate therapy and development of resistance to HIV. HIV counseling and testing should be offered before starting lamivudine tablets (HBV) and periodically during therapy. Inform patients that if they have or develop HIV infection and are not receiving effective HIV treatment, lamivudine tablets (HBV) may increase the risk of development of resistance to HIV medications. Advise patients that lamivudine tablets (HBV) contains a lower dose of the same active ingredient (lamivudine) as HIV drugs containing lamivudine [see Dosage and Administration(2.1), Warnings and Precautions(5.2)].

Emergence of HBV Resistance

Inform patients that emergence of resistant hepatitis B virus and worsening of disease can occur during treatment. Patients should promptly report any new or worsening symptoms to their physician [see Warnings and Precautions (5.3)] .

Lactic Acidosis/Severe Hepatomegaly with Steatosis

Advise patients that lactic acidosis and severe hepatomegaly with steatosis have been reported with use of nucleoside analogues and other antiretrovirals. Advise patients to stop taking lamivudine tablets (HBV) if they develop clinical symptoms suggestive of lactic acidosis or pronounced hepatotoxicity [see Warnings and Precautions(5.4)].

Hepatitis B Transmission

Advise patients that treatment with lamivudine tablets (HBV) has not been shown to reduce the risk of transmission of HBV to others through sexual contact or blood contamination.

Drug Interactions

Inform patients that lamivudine tablets (HBV) may interact with some drugs; therefore, patients should be advised to report to their healthcare provider the use of any prescription or non-prescription medication, or herbal products. Advise patients to avoid chronic use of sorbitol-containing prescription and over-the-counter medicines when possible. Taking lamivudine tablets (HBV) with chronically administered sorbitol-containing medicines may decrease the concentrations of lamivudine [see Drug Interactions (7.2)] .

Pregnancy Registry

Advise patients that there is a pregnancy exposure registry that monitors pregnancy outcomes in women exposed to lamivudine tablets (HBV) during pregnancy [see Use in Specific Populations (8.1)] .

Missed Dosage

Instruct patients that if they miss a dose of lamivudine tablets (HBV), to take it as soon as they remember. Advise patients not to double their next dose or take more than the prescribed dose [see Dosage and Administration (2)] .

All registered trademarks in this document are the property of their respective owners.

APOTEX INC.
LAMIVUDINE TABLETS (HBV)
100 mg

Manufactured by Manufactured for
Apotex Inc. Apotex Corp.
Totonto, Ontario Weston, Florida
Canada M9L 1T9 USA 33326
Revised: February 2022

Revision: 7

Marketed by:
GSMS, Inc.
Camarillo, CA 93012 USA

PATIENT INFORMATION

Lamivudine Tablets (HBV)
(la miv′ ue deen)

What is the most important information I should know about lamivudine tablets (HBV)?

Lamivudine tablets (HBV) can cause serious side effects, including:

- Worsening liver disease.Your hepatitis B infection may become worse after stopping treatment with lamivudine tablets (HBV). Worsening liver disease can be serious and may lead to death. If you stop treatment with lamivudine tablets (HBV), your healthcare provider will need to check your health and do blood tests to check your liver for at least several months after you stop taking lamivudine tablets (HBV).
- Risk of HIV-1 resistance in people with unknown HIV-1 infection or in people with untreated HIV-1 infection. If you have or get HIV-1 (Human Immunodeficiency Virus type 1) that is not being treated with medicines while taking lamivudine tablets (HBV), the HIV-1 virus may develop resistance to certain HIV-1 medicines and become harder to treat .
  Your healthcare provider should offer you counseling and testing for HIV-1 infection before you start treatment for hepatitis B with lamivudine tablets (HBV) and during treatment.
  Lamivudine tablets (HBV) contain a lower dose of lamivudine than other medicines that contain lamivudine and are used to treat HIV-1 infection.
- Resistant Hepatitis B Virus (HBV).The hepatitis B virus can change (mutate) during your treatment with lamivudine tablets (HBV) and become harder to treat (resistant). If this happens, your liver disease can become worse and may lead to death. Tell your healthcare provider right away if you have any new symptoms.
- For more information about side effects, see “What are the possible side effects of lamivudine tablets (HBV) ?”

What is lamivudine tablets (HBV)?

Lamivudine tablets (HBV) is a prescription medicine used to treat long-term (chronic) hepatitis B virus (HBV) when the disease is progressing and there is liver swelling (inflammation).

It is not known if lamivudine tablets (HBV) is safe and effective in:

- people with chronic HBV who have a severely damaged liver that is unable to work properly (decompensated liver disease)
- people with HIV-1, hepatitis C virus, or hepatitis D (delta) virus
- people who have had a liver transplant
- children with chronic HBV less than 2 years of age

Lamivudine tablets (HBV) does not stop you from spreading HBV to others by sex, sharing needles, or being exposed to your blood. Avoid doing things that can spread HBV infection to others.

Do not take lamivudine tablets (HBV):

- If you are allergic to lamivudine or any of the ingredients in lamivudine tablets (HBV). See the end of this Patient Information leaflet for a complete list of ingredients in lamivudine tablets (HBV).

Before taking lamivudine tablets (HBV), tell your healthcare provider about all of your medical conditions, including if you:

- have HIV-1 infection
- have kidney problems
- are pregnant or plan to become pregnant. It is not known if lamivudine tablets (HBV) will harm your unborn baby.
  Pregnancy Registry. There is a pregnancy registry for women who take antiviral medicines during pregnancy. The purpose of this registry is to collect information about the health of you and your baby. Talk to your healthcare provider about how you can take part in this registry.
- are breastfeeding or plan to breastfeed. Lamivudine can pass into your breast milk and may harm your baby. You and your healthcare provider should decide if you will take lamivudine tablets (HBV) or breastfeed.

Tell your healthcare provider about all the medicines you take,including prescription and over-the-counter medicines, vitamins, and herbal supplements. Some medicines interact with lamivudine tablets (HBV). Keep a list of your medicines to show your healthcare provider and pharmacist.

- You can ask your healthcare provider or pharmacist for a list of medicines that interact with lamivudine tablets (HBV).
- Do not start taking a new medicine without telling your healthcare provider.Your healthcare provider can tell you if it is safe to take lamivudine tablets (HBV) with other medicines.

Lamivudine tablets (HBV) should not be taken if you also take other medicines that contain lamivudineor emtricitabine.

How should I take lamivudine tablets (HBV)?

- Take lamivudine tablets (HBV) exactly as your healthcare provider tells you to take it.
- Do not change your dose or stop taking lamivudine tablets (HBV) without talking with your healthcare provider
- If you miss a dose of lamivudine tablets (HBV) , take it as soon as you remember. Do not take 2 doses at the same time or take more than what your healthcare provider tells you to take.
- Stay under the care of a healthcare provider during treatment with lamivudine tablets (HBV)
- Lamivudine tablets (HBV) may be taken with or without food.
- Your healthcare provider may prescribe a lower dose if you have problems with your kidneys.
- For children 2 to 17 years of age, your healthcare provider will prescribe a dose of lamivudine tablets (HBV) based on your child’s body weight.
- Tell your healthcare provider if you or your child has trouble swallowing tablets.
- If you take too much lamivudine tablets (HBV), call your healthcare provider or go to the nearest hospital emergency room right away.

What are the possible side effects of lamivudine tablets (HBV)?

Lamivudine tablets (HBV) may cause serious side effects, including:

- See "What is the most important information I should know about lamivudine tablets (HBV)?"
- Too much lactic acid in your blood (lactic acidosis).Lactic acidosis is a serious medical emergency that can lead to death . Call your healthcare provider right away if you get any of the following symptoms that could be signs of lactic acidosis:
  - feel very weak or tired
  - unusual (not normal) muscle pain
  - trouble breathing
  - stomach pain with nausea and vomiting
  - feel cold, especially in your arms and legs
  - feel dizzy or light-headed
  - have a fast or irregular heartbeat

Severe liver problems.Severe liver problems can happen in people who take lamivudine tablets (HBV) or similar medicines. In some cases, these severe liver problems can lead to death. Your liver may become large (hepatomegaly) and you may develop fat in your liver (steatosis) when you take lamivudine tablets (HBV). Call your healthcare provider right away if you get any of the following signs or symptoms of liver problems:

-
  - your skin or the white part of your eyes turns yellow (jaundice)
  - dark or “tea-colored” urine
  - light-colored stools (bowel movements)
  - loss of appetite for several days or longer
  - nausea
  - pain, aching, or tenderness on the right side of your stomach area

You may be more likely to get lactic acidosis or severe liver problems if you are female or veryoverweight (obese).

The most common side effects of lamivudine tablets (HBV) includeear, nose, and throat infections; sore throat; and diarrhea.

Tell your healthcare provider if you have any side effect that bothers you or that does not go away.

These are not all the possible side effects of lamivudine tablets (HBV).

Call your doctor for medical advice about side effects. You may report side effects to FDA at 1-800-FDA-1088.

How should I store lamivudine tablets (HBV)?

- Store lamivudine tablets (HBV) at room temperature between 68°F to 77°F (20°C to 25°C).

Keep lamivudine tablets (HBV) and all medicines out of the reach of children.

General information about the safe and effective use of lamivudine tablets (HBV)

Medicines are sometimes prescribed for purposes other than those listed in a Patient Information leaflet. Do not use lamivudine tablets (HBV) for a condition for which it was not prescribed. Do not give lamivudine tablets (HBV) to other people, even if they have the same symptoms that you have. It may harm them.

You can ask your pharmacist or healthcare provider for information about lamivudine tablets (HBV) that is written for health professionals.

What are the ingredients in lamivudine tablets (HBV)?

Active ingredient:lamivudine

Inactive ingredients:anhydrous lactose, crospovidone, colloidal silicon dioxide, ferric oxide red, ferric oxide yellow, hypromellose, hydroxypropyl cellulose, magnesium stearate, polyethylene glycol and titanium dioxide.

This Patient Information has been approved by the U.S. Food and Drug Administration

All registered trademarks in this document are the property of their respective owners.

APOTEX INC.
LAMIVUDINE TABLETS (HBV)
100 mg

Manufactured by
Apotex Inc.
Toronto, Ontario
Canada M9L 1T9

Manufactured for
Apotex Corp.
Weston, Florida
USA 33326

Revised: February 2022

Revision: 7

Marketed by:
GSMS, Inc.
Camarillo, CA 93012 USA

PRINCIPAL DISPLAY PANEL

PACKAGE LABEL - PRINCIPAL DISPLAY PANEL - 100 MG LABEL

NDC 51407-866-60

100 mg

Rx only

60 Tablets